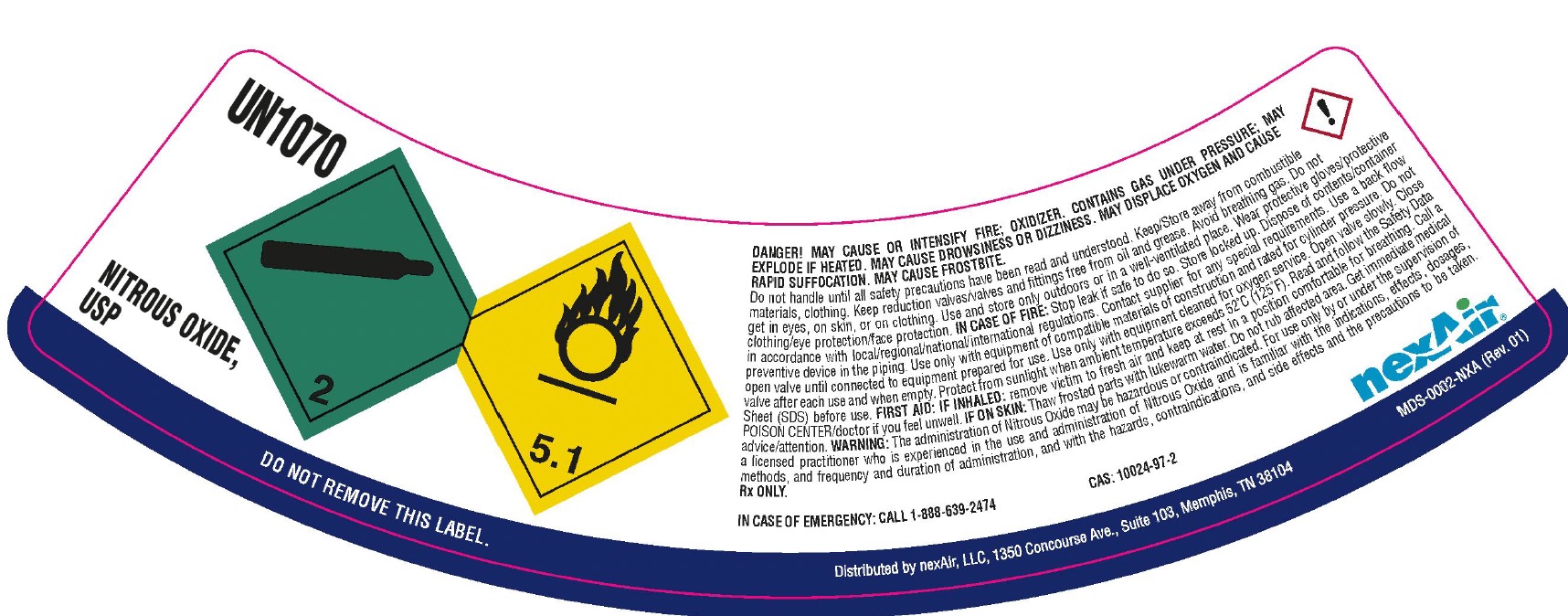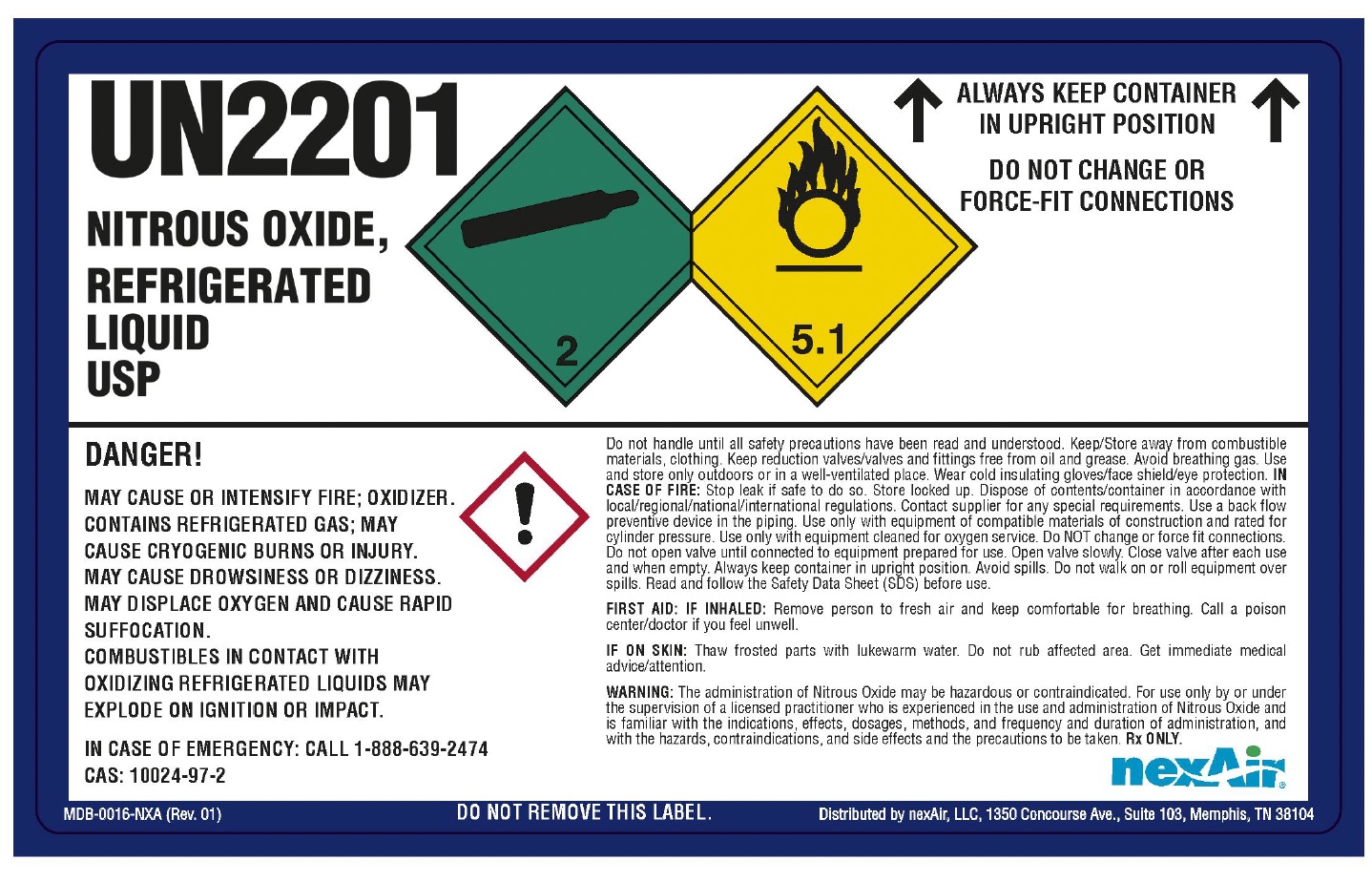 DRUG LABEL: Nitrous Oxide
NDC: 12213-593 | Form: GAS
Manufacturer: NEXAIR, LLC
Category: prescription | Type: HUMAN PRESCRIPTION DRUG LABEL
Date: 20251031

ACTIVE INGREDIENTS: NITROUS OXIDE 990 mL/1 L

nitrous oxide

PACKAGE LABEL

UN1070

NITROUS OXIDE, USP

DO NOT REMOVE THIS LABEL.

DANGER! MAY CAUSE OR INTENSIFY FIRE OXIDIZER. CONTAINS GAS UNDER PRESSURE; MAY EXPLODE IF HEATED. MAY CAUSE DROWSINESS OR DIZZINESS. MAY DISPLACE OXYGEN AND CAUSE RAPID SUFFOCATION. MAY CAUSE FROSTBITE.

Do not handle until all safety precautions have been read and understood. Keep/Store away from combustible materials, clothing. Keep reduction valves/valves and fittings free from oil and grease. Avoid breathing gas. Do not get in eyes, on skin, or on clothing. Use and store only outdoors or in a well-ventilated place. Wear protective gloves/protective clothing/eye protection/face protection. IN CASE OF FIRE: Stop leak if safe to do so. Store locked up. Dispose of contents/container in accordance with local/regional/national/internation regulations. Contact supplier for any special requirements. Use a back flow preventive device in the piping. Use only with equipment of compatible materials of construction and rated for cylinder pressure. Do not open valve until connected to equipment prepared for use. Use only with equipment cleaned for oxygen service. Open valve slowly. Close valve after each use and when empty. Protect from sunlight when ambient temperature exceeds 52 C (125 F). Read and follow the Safety Data Sheet (SD)S before use. FIRST AID: IF INHALED: remove victim to fresh air and keep at rest in a position comfortable for breathing. Call a POISON CENTER/doctor if you feel unwell. IF ON SKIN: Thaw frosted parts with lukewarm water. Do not rub affected area. Get immediate medical advice/attention. WARNING: The administration of Nitrous Oxide may be hazardous or contraindicated. For use only by or under the supervision of a licensed practitioner who is experienced in the use and administration of Nitrous Oxide and is familiar with the indications, effects, dosages, methods, and frequency and duration of administration, and with the hazards, contraindications, and side effects and the precautions to be taken.

Rx ONLY.

IN CASE OF EMERGENCY: CALL 1-888-639-2474 CAS: 10024-97-2

nexAir

Distributed by nexAir, LLC, 1350 Concourse Ave., Suite 103, Memphis, TN 38104

PACKAGE LABEL

UN2201

NITROUS OXIDE, REFRIGERAED LIQUID USP

ALWAYS KEEP CONTAINER IN UPRIGHT POSITION

DO NOT CHANGE OR FORCE-FIT CONNECTIONS

DANGER!

MAY CAUSE OR INTENSIFY FIRE; OXIDIZER. CONTAINS REFRIGERATED GAS; MAY CAUSE CRYOGENIC BURNS OR INJURY. MAY CAUSE DROWSINESS OR DIZZINESS. MAY DISPLACE OXYGEN AND CAUSE RAPID SUFFOCATION. COMBUSTIBLES IN CONTACT WITH OXIDIZING REFRIGERATED LIQUIDS MAY EXPLODE ON IGNITION OR IMPACT.

IN CASE OF EMERGENCY: CALL 1-888-639-2474

CAS: 10024-97-2

Do not handle until all safety precautions have been read and understood. Keep/Store away from combustible materials, clothing. Keep reduction valves/valves and fittings free from oil and grease. Avoid breathing gas. Use and store only outdoors or in a well-ventilated place. Wear cold insulating gloves/face shield/eye protection. IN CASE OF FIRE: Stop leak if safe to do so. Store locked up. Dispose of contents/container in accordance with local/regional/national/international regulations. Contact supplier for any special requirements. Use a back flow preventive device in the piping. Use only with equipment of compatible materials of construction and rated for cylinder pressure. Use only with equipment cleaned for oxygen service. Do NOT change or force fit connections. Do not open valve until connected to equipment prepared for use. Open valve slowly. Close valve after each use and when empty. Always keep container in upright position. Avoid spills. Do not walk on or roll equipment over spills. Read and follow the Safety Data Sheet (SDS) before use.

FIRST AID: IF INHALED: Remove person to fresh air and keep comfortable for breathing. Call a poison center/doctor if you feel unwell.

IF ON SKIN: Thaw frosted parts with lukewarm water. Do not rub affected area. Get immediate medical advice/attention.

WARNING: The administration of Nitrous Oxide may be hazardous or contraindicated. For use only by or under the supervision of a licensed practitioner who is experienced in the use and administration of Nitrous Oxide and is familiar with the indications, effects, dosages, methods, and frequency and duration of administration, and with the hazards, contraindications, and side effects and the precautions to be taken. Rx ONLY

nexAir

Distributed by nexAir, LLC, 1350 Concourse Ave., Suite 103, Memphis, TN 38104